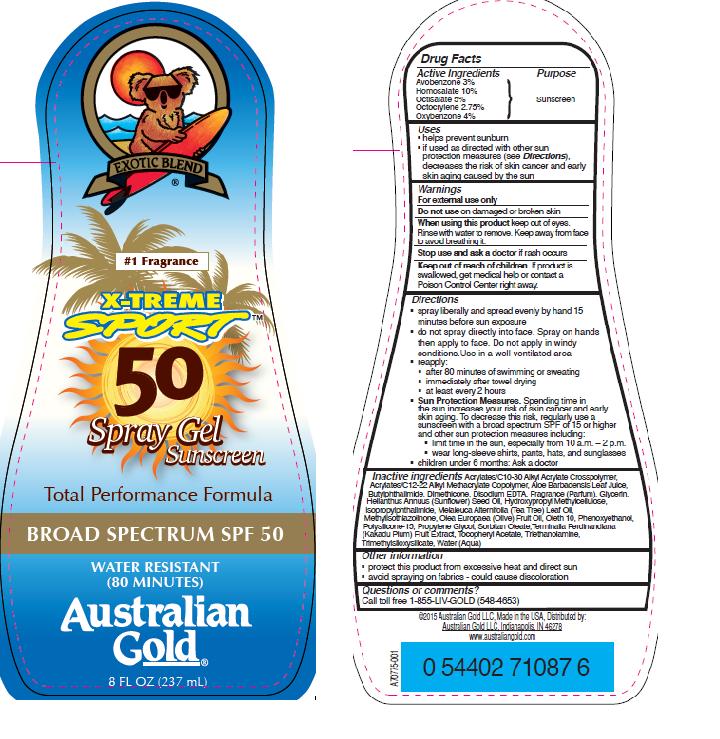 DRUG LABEL: Australian Gold
NDC: 58443-0199 | Form: SPRAY
Manufacturer: Prime Enterprises Inc.
Category: otc | Type: HUMAN OTC DRUG LABEL
Date: 20200117

ACTIVE INGREDIENTS: OXYBENZONE 40.4 mg/1 mL; AVOBENZONE 30.33 mg/1 mL; HOMOSALATE 101.1 mg/1 mL; OCTISALATE 50.55 mg/1 mL; OCTOCRYLENE 27.8 mg/1 mL
INACTIVE INGREDIENTS: TEA TREE OIL; TRIMETHYLSILOXYSILICATE (M/Q 0.6-0.8); EDETATE DISODIUM; GLYCERIN; SUNFLOWER OIL; METHYLISOTHIAZOLINONE; ISOPROPYLPHTHALIMIDE; HYPROMELLOSES; OLIVE OIL; PHENOXYETHANOL; POLYSILICONE-15; PROPYLENE GLYCOL; SORBITAN MONOOLEATE; N-BUTYLPHTHALIMIDE; ALOE VERA LEAF; DIMETHICONE; (C10-C30)ALKYL METHACRYLATE ESTER; KAKADU PLUM; ALPHA-TOCOPHEROL ACETATE; TROLAMINE; WATER; ALKYL (C12-15) BENZOATE

Australian Gold X-Treme Sport SPF 50 Spray Gel Sunscreen

Active Ingredients

Avobenzone 3%

Homosalate 10%

Octisalate 5%

Octocrylene 2.75%

Oxybenzone 4%

Purpose

Sunscreen

Uses

- helps prevent sunburn
- if used as directed with other sun protection measures (see Directions), decreases the risk of skin cancer and early skin aging caused by the sun

WARNINGS

For external use only.

Do not use on damaged or broken skin

When using this product keep out of eyes. Rinse with water to remove.

Stop use and ask a doctor if rash occurs

Keep out of reach of children. If product is swallowed, get medical help or contact a Poison Control Center right away.

Directions

- spray liberally and spread evenly by hand 15 minutes before sun exposure
- do not spray directly into face. Spray on hands then apply to face. Do not apply in windy conditions. Use in a well-ventilated area
- reapply:
- after 80 minutes of swimming or sweating
- immediately after towel drying
- at least every 2 hours
- Sun Protection Measures. Spending time in the sun increases your risk of skin cancer and early skin aging. To decrease this risk, regularly use a sunscreen with broad spectrum SPF of 15 or higher and other sun protection measures including:
- limit time in the sun, especially from 10 a.m. – 2 p.m.
- wear long-sleeve shirts, pants, hats, and sunglasses
- children under 6 months: Ask a doctor

INACTIVE INGREDIENT

Acrylates/C10-30 Alkyl Acrylate Crosspolymer, Acrylates/C12-22 Alkyl Methacrylate Copolymer, Aloe Barbadensis Leaf Juice, Butylphthalimide, Dimethicone, Disodium EDTA, Fragrance (Parfum), Glycerin, Helianthus Annuus (Sunflower) Seed Oil, Hydroxypropyl Methylcellulose, Isopropylphthalimide, Melaleuca Alternifolia (Tea Tree) Leaf Oil, Methylisothiazolinone, Olea Europaea (Olive) Fruit Oil, Phenoxyethanol, Polysilicone-15, Propylene Glycol, Sorbitan Oleate, Terminalia Ferdinandiana (Kakadu Plum) Fruit Extract, Tocopheryl Acetate, Triethanolamine, Trimethylsiloxysilicate, Water (Aqua)

Other Information

- protect this product from excesive heat and direct sun
- avoid spraying on fabrics - could caue discoloration

Questions or Comments?

Call toll free 1-855-LIV-GOLD (548-4653)